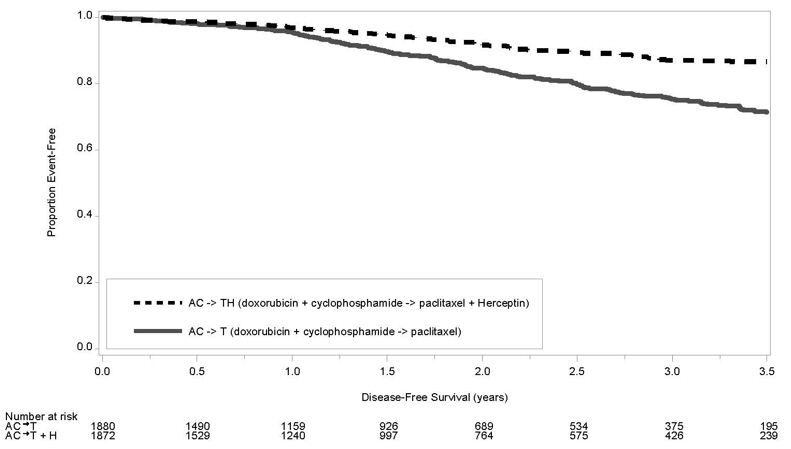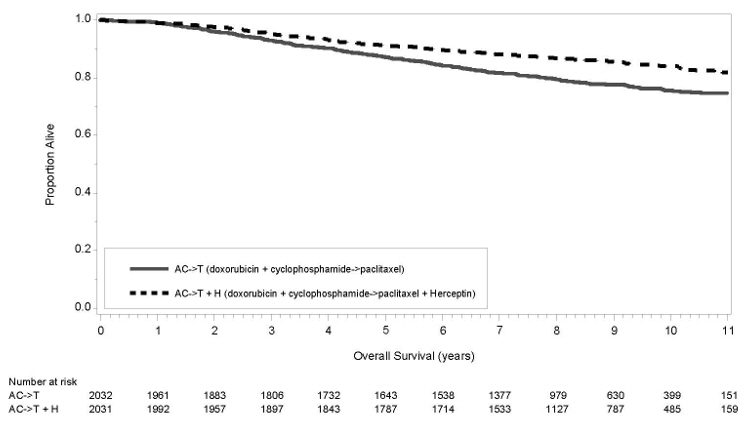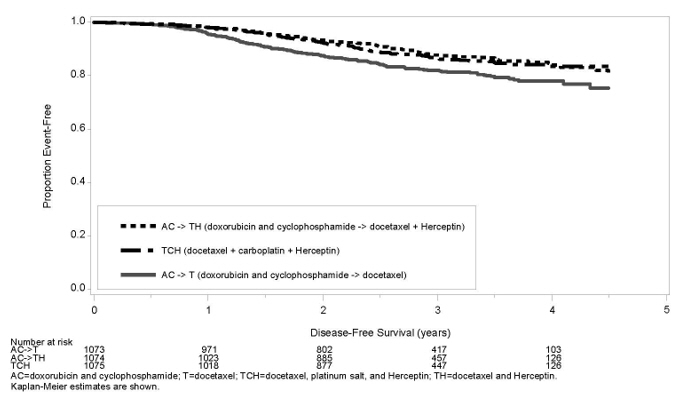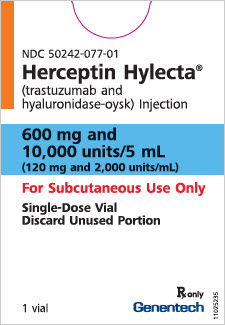 DRUG LABEL: Herceptin Hylecta
NDC: 50242-077 | Form: INJECTION, SOLUTION
Manufacturer: Genentech, Inc.
Category: prescription | Type: HUMAN PRESCRIPTION DRUG LABEL
Date: 20251210

ACTIVE INGREDIENTS: TRASTUZUMAB 600 mg/5 mL; HYALURONIDASE (HUMAN RECOMBINANT) 10000 U/5 mL
INACTIVE INGREDIENTS: HISTIDINE HYDROCHLORIDE MONOHYDRATE 18.35 mg/5 mL; HISTIDINE 1.95 mg/5 mL; TREHALOSE DIHYDRATE 397.25 mg/5 mL; POLYSORBATE 20 2 mg/5 mL; METHIONINE 7.45 mg/5 mL; WATER

HIGHLIGHTS OF PRESCRIBING INFORMATION

These highlights do not include all the information needed to use HERCEPTIN HYLECTA safely and effectively. See full prescribing information for HERCEPTIN HYLECTA.
HERCEPTIN HYLECTA® (trastuzumab and hyaluronidase-oysk) injection, for subcutaneous use
Initial U.S. Approval: 2019

WARNING: CARDIOMYOPATHY, EMBRYO-FETAL TOXICITY, and PULMONARY TOXICITY

See full prescribing information for complete boxed warning.

Cardiomyopathy: HERCEPTIN HYLECTA can result in subclinical and clinical cardiac failure manifesting as CHF, and decreased LVEF, with greatest risk when administered concurrently with anthracyclines. Evaluate cardiac function prior to and during treatment. Discontinue HERCEPTIN HYLECTA for cardiomyopathy. (2.4, 5.1)

Pulmonary Toxicity: Discontinue HERCEPTIN HYLECTA for anaphylaxis, angioedema, interstitial pneumonitis or acute respiratory distress syndrome. (5.3)

Embryo-Fetal Toxicity: Exposure to HERCEPTIN HYLECTA during pregnancy can result in oligohydramnios, in some cases complicated by pulmonary hypoplasia and neonatal death. Advise patients of these risks and the need for effective contraception. (5.2, 8.1, 8.3)

RECENT MAJOR CHANGES

Dosage and Administration, Evaluation and Testing Before Initiating HERCEPTIN HYLECTA (2.1) | 06/2024

1 INDICATIONS AND USAGE

HERCEPTIN HYLECTA is a combination of trastuzumab, a HER2/neu receptor antagonist, and hyaluronidase, an endoglycosidase, indicated in adults for:

- The treatment of HER2-overexpressing breast cancer. (1.1, 1.2)

Select patients for therapy based on an FDA-approved companion diagnostic for trastuzumab. (1, 2.2)

2 DOSAGE AND ADMINISTRATION

For subcutaneous use only. HERCEPTIN HYLECTA has different dosage and administration instructions than intravenous trastuzumab products.

Do not administer intravenously. (2.3)

Do not substitute HERCEPTIN HYLECTA for or with ado-trastuzumab emtansine. (2.3)

Perform HER2 testing using FDA-approved tests by laboratories with demonstrated proficiency. (1, 2.2)

The recommended dose of HERCEPTIN HYLECTA is 600 mg/10,000 units (600 mg trastuzumab and 10,000 units hyaluronidase) administered subcutaneously over approximately 2-5 minutes once every three weeks. (2.3)

3 DOSAGE FORMS AND STRENGTHS

- Injection: 600 mg trastuzumab and 10,000 units hyaluronidase per 5 mL (120 mg/2,000 units per mL) solution in a single-dose vial. (3)

4 CONTRAINDICATIONS

- None. (4)

5 WARNINGS AND PRECAUTIONS

- Exacerbation of Chemotherapy-Induced Neutropenia. (5.4, 6.1)
- Hypersensitivity and Administration-Related Reactions (ARRs): Severe ARRs, including anaphylaxis, have been reported with HERCEPTIN HYLECTA. Monitor patients for systemic hypersensitivity reactions. Permanently discontinue HERCEPTIN HYLECTA in patients who experience anaphylaxis or severe hypersensitivity reactions. (5.5)

6 ADVERSE REACTIONS

Adjuvant Breast Cancer

- Most common adverse reactions (≥10%) for HERCEPTIN HYLECTA are fatigue, arthralgia, diarrhea, injection site reaction, upper respiratory tract infection, rash, myalgia, nausea, headache, edema, flushing, pyrexia, cough, and pain in extremity. (6.1)

Metastatic Breast Cancer (based on intravenous trastuzumab)

- Most common adverse reactions (≥10%) are fever, chills, headache, infection, congestive heart failure, insomnia, cough, and rash. (6.1)

To report SUSPECTED ADVERSE REACTIONS, contact Genentech at 1-888-835-2555 or FDA at 1-800-FDA-1088 or www.fda.gov/medwatch.

8 USE IN SPECIFIC POPULATIONS

Females and Males of Reproductive Potential: Verify the pregnancy status of females prior to initiation of HERCEPTIN HYLECTA. (8.3)

FULL PRESCRIBING INFORMATION

WARNING: CARDIOMYOPATHY, EMBRYO-FETAL TOXICITY, and PULMONARY TOXICITY

Cardiomyopathy

HERCEPTIN HYLECTA administration can result in sub-clinical and clinical cardiac failure. The incidence and severity was highest in patients receiving HERCEPTIN HYLECTA with anthracycline-containing chemotherapy regimens.

Evaluate left ventricular function in all patients prior to and during treatment with HERCEPTIN HYLECTA. Discontinue HERCEPTIN HYLECTA treatment in patients receiving adjuvant therapy and withhold HERCEPTIN HYLECTA in patients with metastatic disease for clinically significant decrease in left ventricular function [see Dosage and Administration (2.4) and Warnings and Precautions (5.1)].

Pulmonary Toxicity

HERCEPTIN HYLECTA administration can result in serious and fatal pulmonary toxicity. Symptoms usually occur during or within 24 hours of HERCEPTIN HYLECTA administration. Discontinue HERCEPTIN HYLECTA for anaphylaxis, angioedema, interstitial pneumonitis, or acute respiratory distress syndrome [see Warnings and Precautions (5.3, 5.5)]. Monitor patients until symptoms completely resolve.

Embryo-Fetal Toxicity

Exposure to HERCEPTIN HYLECTA during pregnancy can result in oligohydramnios and oligohydramnios sequence manifesting as pulmonary hypoplasia, skeletal abnormalities, and neonatal death. Advise patients of these risks and the need for effective contraception [see Warnings and Precautions (5.2) and Use in Specific Populations (8.1, 8.3)].

1 INDICATIONS AND USAGE

1.1 Adjuvant Breast Cancer

HERCEPTIN HYLECTA is indicated for adjuvant treatment of adults with HER2 overexpressing node positive or node negative (ER/PR negative or with one high risk feature [see Clinical Studies (14.1)]) breast cancer:

- as part of a treatment regimen consisting of doxorubicin, cyclophosphamide, and either paclitaxel or docetaxel
- as part of a treatment regimen with docetaxel and carboplatin
- as a single agent following multi-modality anthracycline based therapy.

Select patients for therapy based on an FDA-approved companion diagnostic for trastuzumab [see Dosage and Administration (2.2)].

1.2 Metastatic Breast Cancer

HERCEPTIN HYLECTA is indicated in adults:

- In combination with paclitaxel for first-line treatment of HER2-overexpressing metastatic breast cancer
- As a single agent for treatment of HER2-overexpressing breast cancer in patients who have received one or more chemotherapy regimens for metastatic disease.

Select patients for therapy based on an FDA-approved companion diagnostic for trastuzumab [see Dosage and Administration (2.2)].

2 DOSAGE AND ADMINISTRATION

2.1 Evaluation and Testing Before Initiating HERCEPTIN HYLECTA

Verify the pregnancy status of females of reproductive potential prior to the initiation of HERCEPTIN HYLECTA [see Use in Specific Populations (8.1, 8.3)].

2.2 Patient Selection

Select patients based on HER2 protein overexpression or HER2 gene amplification in tumor specimens [see Indications and Usage (1) and Clinical Studies (14)]. Assessment of HER2 protein overexpression and HER2 gene amplification should be performed using FDA-approved tests specific for breast cancer by laboratories with demonstrated proficiency. Information on the FDA-approved tests for the detection of HER2 protein overexpression and HER2 gene amplification is available at: http://www.fda.gov/CompanionDiagnostics.

Improper assay performance, including use of suboptimally fixed tissue, failure to utilize specified reagents, deviation from specific assay instructions, and failure to include appropriate controls for assay validation, can lead to unreliable results.

2.3 Recommended Dosage

HERCEPTIN HYLECTA is for subcutaneous use only. HERCEPTIN HYLECTA has different dosage and administration instructions than intravenous trastuzumab products. Do not administer intravenously.

Do not substitute HERCEPTIN HYLECTA for or with ado-trastuzumab emtansine.

The recommended dose of HERCEPTIN HYLECTA is 600 mg/10,000 units (600 mg trastuzumab and 10,000 units hyaluronidase) administered subcutaneously over approximately 2-5 minutes once every three weeks.

No loading dose is required. No dose adjustments for patient body weight or for different concomitant chemotherapy regimens are required.

Duration of treatment

Patients with adjuvant breast cancer should be treated with HERCEPTIN HYLECTA for 52 weeks or until disease recurrence, whichever occurs first; extending treatment in adjuvant breast cancer beyond one year is not recommended.

Patients with metastatic breast cancer (MBC) should be treated with HERCEPTIN HYLECTA until progression of disease.

Missed Dose

If one dose is missed, it is recommended to administer the next 600 mg/10,000 units dose (i.e. the missed dose) as soon as possible. The interval between subsequent HERCEPTIN HYLECTA doses should not be less than three weeks.

2.4 Dosage Modification for Adverse Reactions

Cardiomyopathy [see Boxed Warning, Warnings and Precautions (5.1)]

Assess left ventricular ejection fraction (LVEF) prior to initiation of HERCEPTIN HYLECTA and at regular intervals during treatment. Withhold HERCEPTIN HYLECTA dosing for at least 4 weeks for either of the following:

- ≥16% absolute decrease in LVEF from pre-treatment values
- LVEF below institutional limits of normal and ≥10% absolute decrease in LVEF from pretreatment values.

HERCEPTIN HYLECTA may be resumed if, within 4–8 weeks, the LVEF returns to normal limits and the absolute decrease from baseline is ≤15%.

Permanently discontinue HERCEPTIN HYLECTA for a persistent (>8 weeks) LVEF decline or for suspension of HERCEPTIN HYLECTA dosing on more than 3 occasions for cardiomyopathy.

2.5 Administration and Storage

To prevent medication errors, it is important to check the vial labels to ensure that the drug being prepared and administered is HERCEPTIN HYLECTA and not ado-trastuzumab emtansine or intravenous trastuzumab.

HERCEPTIN HYLECTA should be administered by a healthcare professional.

Parenteral drug products should be inspected visually for particulate matter and discoloration prior to administration, whenever solution and container permit. Do not use vial if particulates or discoloration is present. Discard any unused portion remaining in the vial.

HERCEPTIN HYLECTA is for single use only. The 600 mg/10,000 units (600 mg trastuzumab and 10,000 units hyaluronidase) solution is a ready to use solution for injection which does not need to be diluted.

To avoid needle clogging, attach the hypodermic injection needle to the syringe immediately prior to administration followed by volume adjustment to 5 mL. HERCEPTIN HYLECTA is compatible with polypropylene and polycarbonate syringe material and stainless steel transfer and injection needles.

Prepare the dosing syringe in controlled and validated aseptic conditions. After the solution of HERCEPTIN HYLECTA is withdrawn from the vial and into the syringe, replace the transfer needle with a syringe closing cap. Label the syringe with the peel-off sticker.

Administration

The injection site should be alternated between the left and right thigh. New injections should be given at least 2.5 cm from the old previous site on healthy skin and never into areas where the skin is red, bruised, tender, or hard, or areas where there are moles or scars. During the treatment course with HERCEPTIN HYLECTA other medicinal products for subcutaneous administration should preferably be injected at different sites. The dose should be administered subcutaneously over approximately 2 to 5 minutes.

Storage

If the syringe containing HERCEPTIN HYLECTA is not used immediately, then the syringe can be stored in the refrigerator (2°C to 8°C) for up to 24 hours and subsequently at room temperature (20°C to 25°C) for up to 4 hours. Protect from light. Do not shake or freeze.

3 DOSAGE FORMS AND STRENGTHS

HERCEPTIN HYLECTA is a colorless to yellowish, clear to opalescent solution for subcutaneous injection:

- Injection: 600 mg trastuzumab and 10,000 units hyaluronidase per 5 mL (120 mg/2,000 units per mL) in a single-dose vial.

4 CONTRAINDICATIONS

None.

5 WARNINGS AND PRECAUTIONS

5.1 Cardiomyopathy

HERCEPTIN HYLECTA can cause left ventricular cardiac dysfunction, arrhythmias, hypertension, disabling cardiac failure, cardiomyopathy, and cardiac death [see Boxed Warning: Cardiomyopathy]. HERCEPTIN HYLECTA can also cause asymptomatic decline in LVEF.

There is a 4–6 fold increase in the incidence of symptomatic myocardial dysfunction among patients receiving trastuzumab as a single agent or in combination therapy compared with those not receiving trastuzumab. The highest absolute incidence occurs when trastuzumab is administered with an anthracycline. The incidence of symptomatic myocardial dysfunction for intravenous trastuzumab and HERCEPTIN HYLECTA was similar in clinical trials [see Adverse Reactions (6)].

Withhold HERCEPTIN HYLECTA for ≥16% absolute decrease in LVEF from pre-treatment values or an LVEF value below institutional limits of normal and ≥10% absolute decrease in LVEF from pretreatment values [see Dosage and Administration (2.4)]. The safety of continuation or resumption of HERCEPTIN HYLECTA in patients with HERCEPTIN HYLECTA induced left ventricular cardiac dysfunction has not been studied.

Patients who receive anthracycline after stopping HERCEPTIN HYLECTA may also be at increased risk of cardiac dysfunction [see Drug Interactions (7) and Clinical Pharmacology (12.3)].

Cardiac Monitoring

Conduct thorough cardiac assessment, including history, physical examination, and determination of LVEF by echocardiogram or MUGA scan. The following schedule is recommended:

- Baseline LVEF measurement immediately prior to initiation of HERCEPTIN HYLECTA
- LVEF measurements every 3 months during and upon completion of HERCEPTIN HYLECTA
- Repeat LVEF measurement at 4 week intervals if HERCEPTIN HYLECTA is withheld for significant left ventricular cardiac dysfunction [see Dosage and Administration (2.4)]
- LVEF measurements every 6 months for at least 2 years following completion of HERCEPTIN HYLECTA as a component of adjuvant therapy.

HERCEPTIN HYLECTA

In the HannaH study, the overall percentage of patients with at least one cardiac disorder was similar in both study arms: 15% (44/297) of patients in the HERCEPTIN HYLECTA arm and 14% (42/298) of patients in the intravenous trastuzumab arm. The most frequent cardiac adverse reactions were left ventricular dysfunction [3.4% (10/297) and 4.0% (12/298)], tachycardia [2% (6/297) and 3% (9/298)] and palpitations [2% (6/297) and 1.3% (4/298)] in the HERCEPTIN HYLECTA arm and the intravenous trastuzumab arm, respectively. The incidence of cardiac failure and congestive cardiac failure was 1% (3/297) in the HERCEPTIN HYLECTA arm and <1% (1/298) in the intravenous trastuzumab arm. The proportion of patients in each treatment arm with a significant decrease in LVEF defined as a drop of ≥10% points to an LVEF of <50% was comparable between treatment arms [3.8% (11/297) in the HERCEPTIN HYLECTA arm and 4.2% (12/298) in the intravenous trastuzumab arm]. In patients with lower body weights (<59 kg, the lowest body weight quartile) the fixed-dose used in the HERCEPTIN HYLECTA arm was not associated with an increased risk of cardiac events or significant drop in LVEF.

In the SafeHER study, in patients treated with HERCEPTIN HYLECTA, 17% (323/1864) reported a cardiac disorder during the treatment period. Decreased ejection fraction, reported in 4.5% (84/1864) of the patients was the most frequently reported cardiac disorder. Congestive cardiac failure was reported in <1% (10/1864) of patients and <1% (4/1864) of patients reported cardiac failure during the treatment period. One patient reported congestive cardiac failure during the follow-up period. Six percent (111/1864) of the patients treated with HERCEPTIN HYLECTA had an LVEF <50% with a decrease of ≥10 points in LVEF from baseline.

Trastuzumab (intravenous formulation):

In study NSABP B31 (NCT00004067), 15% (158/1031) of patients discontinued intravenous trastuzumab due to clinical evidence of myocardial dysfunction or significant decline in LVEF after a median follow-up duration of 8.7 years in the AC-TH arm. In the HERA study (one-year intravenous trastuzumab treatment; NCT00045032), the number of patients who discontinued intravenous trastuzumab due to cardiac toxicity at 12.6 months median duration of follow-up was 2.6% (44/1678). In the BCIRG006 study (NCT00021255), a total of 2.9% (31/1056) of patients in the TCH arm (1.5% during the chemotherapy phase and 1.4% during the monotherapy phase) and 5.7% (61/1068) of patients in the AC-TH arm (1.5% during the chemotherapy phase and 4.2% during the monotherapy phase) discontinued intravenous trastuzumab due to cardiac toxicity.

Among 64 patients receiving adjuvant chemotherapy (studies NSABP B31 and NCCTG N9831; NCT00005970) who developed congestive heart failure (CHF), one patient died of cardiomyopathy, one patient died suddenly without documented etiology, and 33 patients were receiving cardiac medication at last follow-up. Approximately 24% of the surviving patients had recovery to a normal LVEF (defined as ≥ 50%) and no symptoms on continuing medical management at the time of last follow-up. Incidence of CHF is presented in Table 1. The safety of continuation or resumption of intravenous trastuzumab in patients with trastuzumab-induced left ventricular cardiac dysfunction has not been studied.

Table 1 Incidence of Congestive Heart Failure in Adjuvant Breast Cancer Studies
 |  | Incidence of Congestive Heart Failure % (n)
Study | Regimen | Intravenous Trastuzumab | Control
NSABP B31 & NCCTG N9831 [Median follow-up duration for studies NSABP B31 and NCCTG N9831 combined was 8.3 years in the AC→ paclitaxel+Herceptin arm.] | AC [Anthracycline (doxorubicin) and cyclophosphamide.] →paclitaxel + intravenous trastuzumab | 3.2% (64/2000) [Includes 1 patient with fatal cardiomyopathy and 1 patient with sudden death without documented etiology.] | 1.3% (21/1655)
HERA [Includes NYHA II-IV and cardiac death at 12.6 months median duration of follow-up in the one-year intravenous trastuzumab arm.] | Chemotherapy → intravenous trastuzumab | 2% (30/1678) | 0.3% (5/1708)
BCIRG006 | AC→docetaxel + intravenous trastuzumab | 2% (20/1068) | 0.3% (3/1050)
BCIRG006 | Docetaxel + carboplatin + intravenous trastuzumab | 0.4% (4/1056) | 0.3% (3/1050)

In the HERA study (one-year intravenous trastuzumab treatment), at a median follow-up duration of 8 years, the incidence of severe CHF (NYHA III & IV) was 0.8%, and the rate of mild symptomatic and asymptomatic left ventricular dysfunction was 4.6%.

Table 2 Incidence of Cardiac Dysfunction [Congestive heart failure or significant asymptomatic decrease in LVEF.] in Metastatic Breast Cancer Studies
 |  | Incidence
 |  | NYHA I–IV |  | NYHA III–IV
Study | Event | Intravenous Trastuzumab | Control | Intravenous Trastuzumab | Control
H0648g (AC) [Anthracycline (doxorubicin or epirubicin) and cyclophosphamide.] | Cardiac Dysfunction | 28% | 7% | 19% | 3%
H0648g (paclitaxel) | Cardiac Dysfunction | 11% | 1% | 4% | 1%
H0649g | Cardiac Dysfunction [Includes 1 patient with fatal cardiomyopathy.] | 7% | N/A | 5% | N/A

In the BCIRG006 study, the incidence of NCI-CTC Grade 3/4 cardiac ischemia/infarction was higher in the intravenous trastuzumab containing regimens [AC-TH: 0.3% (3/1068) and TCH: 0.2% (2/1056)] as compared to none in AC-T.

5.2 Embryo-Fetal Toxicity

HERCEPTIN HYLECTA can cause fetal harm when administered to a pregnant woman. In post-marketing reports, use of trastuzumab during pregnancy resulted in cases of oligohydramnios and oligohydramnios sequence manifesting as pulmonary hypoplasia, skeletal abnormalities, and neonatal death.

Verify the pregnancy status of females of reproductive potential prior to the initiation of HERCEPTIN HYLECTA. Advise pregnant women and females of reproductive potential that exposure to HERCEPTIN HYLECTA during pregnancy or within 7 months prior to conception can result in fetal harm. Advise females of reproductive potential to use effective contraception during treatment and for 7 months following the last dose of HERCEPTIN HYLECTA [see Use in Specific Populations (8.1, 8.3) and Clinical Pharmacology (12.3)].

5.3 Pulmonary Toxicity

HERCEPTIN HYLECTA can result in serious and fatal pulmonary toxicity. Pulmonary toxicity includes dyspnea, interstitial pneumonitis, pulmonary infiltrates, pleural effusions, non-cardiogenic pulmonary edema, pulmonary insufficiency and hypoxia, acute respiratory distress syndrome, and pulmonary fibrosis. Patients with symptomatic intrinsic lung disease or with extensive tumor involvement of the lungs, resulting in dyspnea at rest, appear to have more severe toxicity.

5.4 Exacerbation of Chemotherapy-Induced Neutropenia

HERCEPTIN HYLECTA may exacerbate chemotherapy-induced neutropenia. In randomized, controlled clinical trials with intravenous trastuzumab, the per-patient incidences of NCI-CTC Grade 3–4 neutropenia and of febrile neutropenia were higher in patients receiving trastuzumab in combination with myelosuppressive chemotherapy as compared to those who received chemotherapy alone. The incidence of septic death was similar among patients who received trastuzumab and those who did not [see Adverse Reactions (6.1)].

5.5 Hypersensitivity and Administration-Related Reactions

Severe administration-related reactions (ARRs), including hypersensitivity and anaphylaxis, have been reported with HERCEPTIN HYLECTA. Patients experiencing dyspnea at rest due to complications of advanced malignancy and comorbidities may be at increased risk of a severe or of a fatal ARR.

In the HannaH and SafeHER trials, 9% and 4.2% of patients experienced Grade 1-4 hypersensitivity and anaphylaxis, respectively. Grade 3-4 hypersensitivity and anaphylactic reactions occurred in 1% and <1% of the patients treated with HERCEPTIN HYLECTA, respectively. In the SafeHER trial, 2 patients required permanent treatment discontinuation with HERCEPTIN HYLECTA (1 patient due to a hypersensitivity reaction and 1 patient due to anaphylaxis). Serious and fatal reactions have been reported after treatment with intravenous trastuzumab products.

Closely monitor patients for systemic hypersensitivity reactions, especially during the first administration. Permanently discontinue HERCEPTIN HYLECTA in patients who experience anaphylaxis or severe hypersensitivity reactions. Medications to treat such reactions, as well as emergency equipment, should be available for immediate use. For patients experiencing reversible Grade 1 or 2 hypersensitivity reactions, consider pre-medication with an analgesic, antipyretic, or an antihistamine prior to readministration of HERCEPTIN HYLECTA [see Adverse Reactions (6.1)].

6 ADVERSE REACTIONS

The following adverse reactions are discussed in greater detail in other sections of the label:

- Cardiomyopathy [see Warnings and Precautions (5.1)]
- Embryo-Fetal Toxicity [see Warnings and Precautions (5.2)]
- Pulmonary Toxicity [see Warnings and Precautions (5.3)]
- Exacerbation of Chemotherapy-Induced Neutropenia [see Warnings and Precautions (5.4)]
- Hypersensitivity and Administration-Related Reactions [see Warnings and Precautions (5.5)]

6.1 Clinical Trials Experience

Because clinical trials are conducted under widely varying conditions, adverse reaction rates observed in the clinical trials of a drug cannot be directly compared to rates in the clinical trials of another drug and may not reflect the rates observed in practice.

The safety of HERCEPTIN HYLECTA administered subcutaneously has been established in the HannaH and SafeHER studies conducted in patients with HER2 overexpressing breast cancer. The safety of intravenous trastuzumab has been established in studies H0648g and H0649g conducted in patients with HER2 overexpressing metastatic breast cancer.

Adjuvant Breast Cancer

HannaH

HannaH was a randomized, open-label study to compare the pharmacokinetics, efficacy, and safety of HERCEPTIN HYLECTA compared to intravenous trastuzumab in women with HER2-positive breast cancer. Patients randomized to the HERCEPTIN HYLECTA arm received a dose of 600 mg HERCEPTIN HYLECTA every 3 weeks throughout the treatment phase. Patients were treated for 8 cycles in combination with chemotherapy (docetaxel followed by 5FU, epirubicin and cyclophosphamide), then underwent surgery, and continued HERCEPTIN HYLECTA to complete 18 cycles of therapy. The median age of patients was 50 (range: 25-81 years), all patients were female, and a majority of patients were white (67%). The median number of HERCEPTIN HYLECTA cycles received was 18 (range 1-18).

The most common adverse reactions of any grade (occurring in ≥10% of patients) with HERCEPTIN HYLECTA were alopecia (63%), nausea (49%), ARRs (48%), neutropenia (44%), diarrhea (34%), asthenia (25%), fatigue (24%), vomiting (23%), myalgia (21%), decreased appetite (20%), stomatitis (19%), arthralgia (18%), headache (17%), rash (16%), constipation (14%), radiation skin injury (14%), pyrexia (12%), cough (12%), anemia (11%), dyspnea (11%), incision site pain (11%), peripheral sensory neuropathy (11%), leukopenia (10%), mucosal inflammation (10%), hot flush (10%), upper respiratory tract infection (10%).

The most common Grade ≥3 adverse reactions (occurring in >1% of patients) in the HERCEPTIN HYLECTA arm were neutropenia (30%), febrile neutropenia (6%), leukopenia (4%), diarrhea (3%), hypertension (2%), irregular menstruation (2%), alopecia (1%), nausea (1%), granulocytopenia (1%), vomiting (1%), amenorrhea (1%), and cellulitis (1%). Adverse reactions leading to interruption of any study drug in the HERCEPTIN HYLECTA arm occurred in 34% of patients; 31% of patients had these events during the neoadjuvant phase of the study with concurrent chemotherapy and 9% of patients had these events during the adjuvant phase. Overall, the most common (≥ 1%) were neutropenia (21%), leukopenia (2.4%), ALT increase (1.7%), pyrexia (1.7%), anemia (1%), bronchitis (1%), and left ventricular dysfunction (1%). Adverse reactions that led to discontinuation of any study drug in the HERCEPTIN HYLECTA arm (>1 patient) were left ventricular dysfunction (2%).

The incidence of ARRs in the HERCEPTIN HYLECTA arm was 48% and was 37% in the intravenous trastuzumab arm. Five (2%) patients in the HERCEPTIN HYLECTA arm experienced a Grade 3 ARR. Three of the events in the HERCEPTIN HYLECTA arm occurred on the day of study drug administration when docetaxel treatment was administered concurrently. The most commonly reported ARRs in the HERCEPTIN HYLECTA arm (≥5% of patients) were rash, pruritus, erythema, cough and dyspnea. Grade 1 and 2 injection-site reactions (ISRs) occurred in 10% of patients in the HERCEPTIN HYLECTA arm. The most common ISRs were injection-site pain and injection-site erythema.

The data in Table 3 were obtained from the HannaH trial for adverse reactions that occurred in ≥ 5% of the patients treated with HERCEPTIN HYLECTA.

Table 3 Adverse Reactions [Contains grouped terms] (≥ 5% Incidence) Reported in HannaH
Adverse Reactions | HERCEPTIN HYLECTA 600 mg n=297 |  | Intravenous Trastuzumab (loading dose: 8 mg/kg; maintenance dose: 6 mg/kg) n=298
 | All Grades % | Grades 3 to 5 % | All Grades % | Grades 3 to 5 %
SKIN AND SUBCUTANEOUS TISSUE DISORDERS
Alopecia, [The HannaH trial was not designed to demonstrate a statistically significant difference in adverse reaction rates between HERCEPTIN HYLECTA and intravenous trastuzumab.] | 63 | 1.3 | 63 | 1.7
Rash, | 26 | < 1 | 26 | -
Nail Disorder, | 14 | - | 14 | < 1
Pruritus, | 9 | - | 9 | -
Skin Discoloration | 9 | - | 8 | -
Erythema | 7 | < 1 | 3 | -
GASTROINTESTINAL DISORDERS
Nausea | 49 | 1.3 | 49 | 1.3
Diarrhea, | 34 | 2.7 | 37 | 2.7
Vomiting | 23 | 1 | 23 | 1.7
Stomatitis | 21 | < 1 | 18 | < 1
Abdominal Pain, | 14 | - | 14 | < 1
Dyspepsia | 11 | - | 10 | -
GENERAL DISORDERS AND ADMINISTRATION SITE CONDITIONS
Fatigue, | 46 | < 1 | 49 | 2
Edema, | 14 | - | 15 | -
Pyrexia | 13 | 1 | 12 | < 1
Mucosal Inflammation | 10 | < 1 | 13 | -
Pain, | 5 | - | 8 | < 1
Injection Site Reaction, [Injection Site Reaction includes terms for injection related reaction and injection site joint pain, bruising, dermatitis, discoloration, discomfort, erythema, extravasation, fibrosis, hematoma, hemorrhage, hypersensitivity, induration, inflammation, irritation, macule, mass, nodule, edema, pallor, paraesthesia, pruritus, rash, reaction, swelling, ulcer, vesicles and warmth.] | 10 | - | < 1 | -
BLOOD AND LYMPHATIC SYSTEM DISORDERS
Neutropenia | 44 | 30 | 47 | 34
Leukopenia, | 11 | 5 | 16 | 8
Anemia, | 12 | < 1 | 14 | 1
Febrile Neutropenia | 6 | 6 | 4 | 4
INFECTIONS AND INFESTATIONS
Upper Respiratory Tract Infection, | 24 | 1 | 27 | < 1
Urinary Tract Infection, | 4 | - | 8 | < 1
MUSCULOSKELETAL AND CONNECTIVE TISSUE DISORDERS
Myalgia | 21 | - | 19 | < 1
Arthralgia, | 18 | - | 21 | < 1
Back Pain | 11 | 1 | 9 | 1
Pain in Extremity | 10 | - | 9 | < 1
Pain, | 8 | < 1 | 9 | -
Bone Pain | 6 | < 1 | 3.4 | -
NERVOUS SYSTEM DISORDERS
Neuropathy Peripheral | 20 | - | 15 | -
Headache | 17 | < 1 | 15 | < 1
Dizziness | 10 | < 1 | 9 | < 1
Dysgeusia | 10 | - | 8 | -
INJURY, POISONING AND PROCEDURAL COMPLICATIONS
Incision Site Complication | 11 | - | 8 | < 1
Pain | 6 | - | 5 | < 1
RESPIRATORY, THORACIC AND MEDIASTINAL DISORDERS
Cough | 12 | < 1 | 8 | -
Dyspnea, | 7 | - | 8 | -
Epistaxis | 6 | - | 6 | -
Nasal Inflammation / Discomfort, | 5 | - | 7 | -
VASCULAR DISORDERS
Flushing | 14 | < 1 | 13 | < 1
Hypertension | 8 | 2.4 | 5 | < 1
METABOLISM AND NUTRITION DISORDERS
Decreased Appetite | 20 | < 1 | 20 | < 1
INVESTIGATIONS
Liver Function Analysis Abnormal, | 6 | 1 | 9 | 1.7
CARDIAC DISORDERS
Arrhythmia | 5 | - | 5 | < 1
IMMUNE SYSTEM DISORDERS
Hypersensitivity, | 7 | 1 | 7 | 1.3

SafeHER

SafeHER was a prospective, two-cohort, non-randomized, multi-center, multinational, open-label study to assess the safety of HERCEPTIN HYLECTA in patients with operable HER2-positive breast cancer. In SafeHER, 1864 patients were enrolled and treated with 600 mg of HERCEPTIN HYLECTA administered subcutaneously once every three weeks for 18 cycles.

The median age of patients was 54 (range: 20-88 years), 99.8% were female, and a majority were white (76%). A majority of the patients received HERCEPTIN HYLECTA concurrently with a chemotherapy regimen (58%). The median number of HERCEPTIN HYLECTA cycles administered was 18 and the median duration of HERCEPTIN HYLECTA exposure was 11.8 months. The median duration of follow-up was 23.7 months.

During the treatment period, the most common adverse reactions of any grade (occurring in ≥10% of patients) were ARRs (39%), diarrhea (21%), fatigue (21%), arthralgia (21%), nausea (15%), myalgia (14%), headache (13%), asthenia (12%), pain in extremity (11%), cough (11%), pyrexia (11%), hot flush (10%), and rash (10%). The most common Grade ≥3 adverse reactions (occurring in >1% of patients) were neutropenia (4%), febrile neutropenia (2%), hypertension (2%), leukopenia (1%), and diarrhea (1%). Adverse reactions that led to study drug discontinuation (≥0.5% of patients) were ejection fraction decreased (2%) and left ventricular dysfunction (1%).

The incidence of ARRs was 39%, with Grade ≥3 ARRs reported in 1% of patients treated with HERCEPTIN HYLECTA. The most frequently reported Grade ≥3 ARRs were dyspnea (<1%), cough (<1%), erythema (<1%), rash (<1%), and drug hypersensitivity (<1%). ISRs were reported in 20% of patients treated with HERCEPTIN HYLECTA. The most common ISRs were injection-site erythema (7%) and injection-site pain (6%). All ISRs were Grade 1 or 2, except for one (<1%) Grade 3 injection site discomfort.

The data in Table 4 were obtained from the SafeHER trial for adverse reactions that occurred in ≥5% of the patients treated with HERCEPTIN HYLECTA.

Table 4 Adverse Reactions [Contains grouped terms] (≥ 5% Incidence) Reported in SafeHER
Adverse Reactions , [Includes adverse reactions reported throughout study treatment and follow-up.] | HERCEPTIN HYLECTA 600 mg (once every 3 weeks) n=1864
Adverse Reactions , [Includes adverse reactions reported throughout study treatment and follow-up.] | All Grades % | Grades 3 to 5 %
GENERAL DISORDERS AND ADMINISTRATION SITE CONDITIONS
Fatigue | 33 | < 1
Injection Site Reaction, [ISR includes injection related reaction and injection site joint pain, bruising, dermatitis, discoloration, discomfort, erythema, extravasation, fibrosis, hematoma, hemorrhage, hypersensitivity, induration, inflammation, irritation, macule, mass, nodule, edema, pallor, paresthesia, pruritus, rash, reaction, swelling, ulcer, vesicles and warmth.] | 20 | < 1
Edema | 12 | < 1
Pyrexia | 11 | < 1
Pain | 8 | < 1
Mucosal Inflammation | 6 | < 1
MUSCULOSKELETAL AND CONNECTIVE TISSUE DISORDERS
Arthralgia | 21 | < 1
Myalgia | 17 | < 1
Pain in Extremity | 11 | < 1
Back Pain | 8 | < 1
Pain | 7 | < 1
GASTROINTESTINAL DISORDERS
Diarrhea | 21 | 1
Nausea | 15 | < 1
Abdominal Pain | 10 | < 1
Constipation | 9 | < 1
Stomatitis | 8 | < 1
Vomiting | 7 | < 1
SKIN AND SUBCUTANEOUS TISSUE DISORDERS
Rash | 17 | < 1
Nail Disorder | 10 | < 1
Alopecia | 9 | < 1
Erythema | 9 | < 1
Pruritus | 6 | -
INFECTIONS AND INFESTATIONS
Upper Respiratory Tract Infection | 19 | < 1
Urinary Tract Infection | 6 | < 1
Viral Infection | 5 | -
NERVOUS SYSTEM DISORDERS
Neuropathy Peripheral | 14 | < 1
Headache | 13 | < 1
Dizziness | 6 | < 1
Paresthesia | 6 | < 1
RESPIRATORY, THORACIC AND MEDIASTINAL DISORDERS
Cough | 11 | < 1
Dyspnea | 8 | < 1
Epistaxis | 6 | -
Nasal Inflammation/Discomfort | 6 | -
VASCULAR DISORDERS
Flushing | 12 | < 1
Hypertension | 8 | 2
BLOOD AND LYMPHATIC SYSTEM DISORDERS
Anemia | 8 | < 1
Neutropenia | 6 | 4
PSYCHIATRIC DISORDERS
Insomnia | 7 | < 1

Metastatic Breast Cancer (based on intravenous trastuzumab)

The data below reflect exposure to intravenous trastuzumab in one randomized, open-label study, H0648g, of chemotherapy with (n=235) or without (n=234) intravenous trastuzumab in patients with metastatic breast cancer, and one single-arm study (H0649g; n=222) in patients with metastatic breast cancer. Data in Table 5 are based on H0648g and H0649g.

Among the 464 patients treated in H0648g, the median age was 52 years (range: 25–77 years). Eighty-nine percent were white, 5% black, 1% Asian, and 5% other racial/ethnic groups. All patients received 4 mg/kg initial dose of intravenous trastuzumab followed by 2 mg/kg weekly. The percentages of patients who received intravenous trastuzumab treatment for ≥ 6 months and ≥ 12 months were 58% and 9%, respectively.

Among the 352 patients treated in single agent studies (213 patients from H0649g), the median age was 50 years (range 28–86 years), 86% were white, 3% were black, 3% were Asian, and 8% in other racial/ethnic groups. Most of the patients received 4 mg/kg initial dose of intravenous trastuzumab followed by 2 mg/kg weekly. The percentages of patients who received intravenous trastuzumab treatment for ≥ 6 months and ≥ 12 months were 31% and 16%, respectively.

Table 5 Adverse Reactions (≥ 5%) in the Intravenous Trastuzumab Arm (H0648g and H0649g)
 | Intravenous trastuzumab [Data for Herceptin single agent were from 4 studies, including 213 patients from H0649g.] n = 352 % | Intravenous trastuzumab + Paclitaxel n = 91 % | Paclitaxel n = 95 % | Intravenous trastuzumab + AC [Anthracycline (doxorubicin or epirubicin) and cyclophosphamide.] n = 143 % | AC n = 135 %
General
Pain | 47 | 61 | 62 | 57 | 42
Asthenia | 42 | 62 | 57 | 54 | 55
Fever | 36 | 49 | 23 | 56 | 34
Chills | 32 | 41 | 4 | 35 | 11
Headache | 26 | 36 | 28 | 44 | 31
Abdominal pain | 22 | 34 | 22 | 23 | 18
Back pain | 22 | 34 | 30 | 27 | 15
Infection | 20 | 47 | 27 | 47 | 31
Flu syndrome | 10 | 12 | 5 | 12 | 6
Accidental injury | 6 | 13 | 3 | 9 | 4
Allergic reaction | 3 | 8 | 2 | 4 | 2
Gastrointestinal
Nausea | 33 | 51 | 9 | 76 | 77
Diarrhea | 25 | 45 | 29 | 45 | 26
Vomiting | 23 | 37 | 28 | 53 | 49
Anorexia | 14 | 24 | 16 | 31 | 26
Nausea and vomiting | 8 | 14 | 11 | 18 | 9
Respiratory
Cough increased | 26 | 41 | 22 | 43 | 29
Dyspnea | 22 | 27 | 26 | 42 | 25
Rhinitis | 14 | 22 | 5 | 22 | 16
Pharyngitis | 12 | 22 | 14 | 30 | 18
Sinusitis | 9 | 21 | 7 | 13 | 6
Skin
Rash | 18 | 38 | 18 | 27 | 17
Herpes simplex | 2 | 12 | 3 | 7 | 9
Acne | 2 | 11 | 3 | 3 | < 1
Nervous
Insomnia | 14 | 25 | 13 | 29 | 15
Dizziness | 13 | 22 | 24 | 24 | 18
Paresthesia | 9 | 48 | 39 | 17 | 11
Depression | 6 | 12 | 13 | 20 | 12
Peripheral neuritis | 2 | 23 | 16 | 2 | 2
Neuropathy | 1 | 13 | 5 | 4 | 4
Metabolic
Peripheral edema | 10 | 22 | 20 | 20 | 17
Edema | 8 | 10 | 8 | 11 | 5
Cardiovascular
Congestive heart failure | 7 | 11 | 1 | 28 | 7
Tachycardia | 5 | 12 | 4 | 10 | 5
Musculoskeletal
Bone pain | 7 | 24 | 18 | 7 | 7
Arthralgia | 6 | 37 | 21 | 8 | 9
Urogenital
Urinary tract infection | 5 | 18 | 14 | 13 | 7
Blood and Lymphatic
Anemia | 4 | 14 | 9 | 36 | 26
Leukopenia | 3 | 24 | 17 | 52 | 34

6.2 Postmarketing Experience

The following adverse reactions have been identified during post-approval use of trastuzumab. Because these reactions are reported voluntarily from a population of uncertain size, it is not always possible to reliably estimate their frequency or establish a causal relationship to drug exposure.

- Administration-related reaction [see Warnings and Precautions (5.5)]
- Oligohydramnios or oligohydramnios sequence, including pulmonary hypoplasia, skeletal abnormalities, and neonatal death [see Warnings and Precautions (5.2)]
- Glomerulopathy [see Adverse Reactions (6.1)]
- Immune thrombocytopenia
- Tumor lysis syndrome (TLS): Cases of possible TLS have been reported in patients treated with trastuzumab. Patients with significant tumor burden (e.g. bulky metastases) may be at a higher risk. Patients could present with hyperuricemia, hyperphosphatemia, and acute renal failure which may represent possible TLS. Providers should consider additional monitoring and/or treatment as clinically indicated.

7 DRUG INTERACTIONS

Anthracyclines

Patients who receive anthracycline after stopping HERCEPTIN HYLECTA may be at increased risk of cardiac dysfunction because of HERCEPTIN HYLECTA's estimated long washout period [see Clinical Pharmacology (12.3)]. If possible, avoid anthracycline-based therapy for up to 7 months after stopping HERCEPTIN HYLECTA. If anthracyclines are used, closely monitor the patient's cardiac function.

8 USE IN SPECIFIC POPULATIONS

8.1 Pregnancy

Pregnancy Pharmacovigilance Program

There is a pregnancy pharmacovigilance program for HERCEPTIN HYLECTA. If HERCEPTIN HYLECTA is administered during pregnancy, or if a patient becomes pregnant while receiving HERCEPTIN HYLECTA or within 7 months following the last dose of HERCEPTIN HYLECTA, health care providers and patients should immediately report HERCEPTIN HYLECTA exposure to Genentech at 1-888-835-2555.

Risk Summary

HERCEPTIN HYLECTA can cause fetal harm when administered to a pregnant woman. In post-marketing reports and published literature, use of trastuzumab during pregnancy resulted in cases of oligohydramnios and of oligohydramnios sequence, manifesting as pulmonary hypoplasia, skeletal abnormalities, and neonatal death [see Data]. Apprise the patient of the potential risks to a fetus. There are clinical considerations if HERCEPTIN HYLECTA is used in a pregnant woman or if a patient becomes pregnant within 7 months following the last dose of HERCEPTIN HYLECTA [see Clinical Considerations].

The background risk of major birth defects and miscarriage for the indicated population is unknown. In the U.S. general population, the estimated background risk of major birth defects and miscarriage in clinically recognized pregnancies is 2% to 4% and 15% to 20%, respectively.

Clinical Considerations

Fetal/Neonatal Adverse Reactions

Monitor women who received HERCEPTIN HYLECTA during pregnancy or within 7 months prior to conception for oligohydramnios. If oligohydramnios occurs, perform fetal/neonatal testing that is appropriate for gestational age and consistent with community standards of care.

Data

Human Data

In post-marketing reports and published literature, use of trastuzumab during pregnancy resulted in cases of oligohydramnios and of oligohydramnios sequence. Fetal manifestations included pulmonary hypoplasia, skeletal abnormalities, and neonatal death. These case reports described oligohydramnios in pregnant women who received trastuzumab either alone or in combination with chemotherapy. In most reported cases, amniotic fluid index increased after use of trastuzumab was stopped. In reported cases where Herceptin therapy was resumed after amniotic index improved, oligohydramnios recurred.

Animal Data

HERCEPTIN HYLECTA for subcutaneous injection contains trastuzumab and hyaluronidase [see Description (11)].

Trastuzumab:

In studies where intravenous trastuzumab was administered to pregnant cynomolgus monkeys during the period of organogenesis at doses up to 25 mg/kg given twice weekly (up to 25 times the recommended weekly human dose of 2 mg/kg), trastuzumab crossed the placental barrier during the early (Gestation Days 20 to 50) and late (Gestation Days 120 to 150) phases of gestation. The resulting concentrations of trastuzumab in fetal serum and amniotic fluid were approximately 33% and 25%, respectively, of those present in the maternal serum but were not associated with adverse developmental effects.

Hyaluronidase:

In an embryo-fetal study, mice have been dosed daily by subcutaneous injection during the period of organogenesis with hyaluronidase (recombinant human) at dose levels up to 2,200,000 U/kg, which is >7,200 times higher than the human dose. The study found no evidence of teratogenicity. Reduced fetal weight and increased numbers of fetal resorptions were observed, with no effects found at a daily dose of 360,000 U/kg, which is >1,200 times higher than the human dose.

In a peri-and post-natal reproduction study, mice have been dosed daily by subcutaneous injection, with hyaluronidase (recombinant human) from implantation through lactation and weaning at dose levels up to 1,100,000 U/kg, which is >3,600 times higher than the human dose. The study found no adverse effects on sexual maturation, learning and memory or fertility of the offspring.

8.2 Lactation

Risk Summary

There is no information regarding the presence of trastuzumab or hyaluronidase in human milk, the effects on the breastfed infant, or the effects on milk production. Published data suggest human IgG is present in human milk but does not enter the neonatal and infant circulation in substantial amounts.

Trastuzumab was present in the milk of lactating cynomolgus monkeys but not associated with neonatal toxicity (see Data). Consider the developmental and health benefits of breastfeeding along with the mother's clinical need for HERCEPTIN HYLECTA treatment and any potential adverse effects on the breastfed child from HERCEPTIN HYLECTA or from the underlying maternal condition. This consideration should also take into account the trastuzumab wash out period of 7 months [see Clinical Pharmacology 12.3].

Data

In lactating cynomolgus monkeys, trastuzumab was present in breast milk at about 0.3% of maternal serum concentrations after pre- (beginning Gestation Day 120) and post-partum (through Post-partum Day 28) doses of 25 mg/kg administered twice weekly (25 times the recommended weekly human dose of 2 mg/kg of intravenous trastuzumab). Infant monkeys with detectable serum levels of trastuzumab did not exhibit any adverse effects on growth or development from birth to 1 month of age.

8.3 Females and Males of Reproductive Potential

Pregnancy Testing

Verify the pregnancy status of females of reproductive potential prior to the initiation of HERCEPTIN HYLECTA.

Contraception

Females

HERCEPTIN HYLECTA can cause embryo-fetal harm when administered during pregnancy. Advise females of reproductive potential to use effective contraception during treatment with HERCEPTIN HYLECTA and for 7 months following the last dose of HERCEPTIN HYLECTA [see Use in Specific Populations (8.1) and Clinical Pharmacology (12.3)].

8.4 Pediatric Use

The safety and effectiveness of HERCEPTIN HYLECTA in pediatric patients have not been established.

8.5 Geriatric Use

Of the total number of patients in the HannaH and SafeHER studies treated with HERCEPTIN HYLECTA, 19% were 65 and over, while 4.7% were 75 and over.

In patients receiving intravenous trastuzumab, the risk of cardiac dysfunction was increased in geriatric patients as compared to younger patients, in both those receiving treatment for adjuvant therapy or metastatic disease. Other differences in safety or effectiveness were not observed between elderly patients and younger patients.

11 DESCRIPTION

HERCEPTIN HYLECTA is a combination of trastuzumab and hyaluronidase. Trastuzumab is a humanized IgG1 kappa monoclonal antibody that selectively binds with high affinity to the extracellular domain of the human epidermal growth factor receptor 2 protein, HER2. Trastuzumab is produced by recombinant DNA technology in a mammalian cell (Chinese Hamster Ovary) culture. Trastuzumab has a molecular weight of approximately 148 kDa.

Hyaluronidase (recombinant human) is an endoglycosidase used to increase the dispersion and absorption of co-administered drugs when administered subcutaneously. It is a glycosylated single-chain protein produced by mammalian (Chinese Hamster Ovary) cells containing a DNA plasmid encoding for a soluble fragment of human hyaluronidase (PH20). Hyaluronidase (recombinant human) has a molecular weight of approximately 61 kDa.

HERCEPTIN HYLECTA (trastuzumab and hyaluronidase) injection is a sterile, preservative-free, colorless to yellowish, clear to opalescent solution supplied in single-dose vials for subcutaneous administration.

HERCEPTIN HYLECTA is supplied as 600 mg trastuzumab and 10,000 units hyaluronidase per 5 mL in single-dose vials. Each mL of solution contains trastuzumab (120 mg), hyaluronidase (2,000 units), L-histidine (0.39 mg), L-histidine hydrochloride monohydrate (3.67 mg), L-methionine (1.49 mg), polysorbate 20 (0.4 mg), α,α-trehalose dihydrate (79.45 mg), and Water for Injection.

12 CLINICAL PHARMACOLOGY

12.1 Mechanism of Action

The HER2 (or c-erbB2) proto-oncogene encodes a transmembrane receptor protein of 185 kDa, which is structurally related to the epidermal growth factor receptor. Trastuzumab has been shown, in both in vitro assays and in animals, to inhibit the proliferation of human tumor cells that overexpress HER2.

Trastuzumab is a mediator of antibody-dependent cellular cytotoxicity (ADCC). In vitro, trastuzumab-mediated ADCC has been shown to be preferentially exerted on HER2 overexpressing cancer cells compared with cancer cells that do not overexpress HER2.

Hyaluronan is a polysaccharide found in the extracellular matrix of the subcutaneous tissue. It is depolymerized by the naturally occurring enzyme hyaluronidase. Unlike the stable structural components of the interstitial matrix, hyaluronan has a half-life of approximately 0.5 days. Hyaluronidase increases permeability of the subcutaneous tissue by depolymerizing hyaluronan. In the doses administered, hyaluronidase in HERCEPTIN HYLECTA acts transiently and locally.

The effects of hyaluronidase are reversible and permeability of the subcutaneous tissue is restored within 24 to 48 hours.

Hyaluronidase has been shown to increase the absorption rate of a trastuzumab product into the systemic circulation when given in the subcutis of Göttingen Minipigs.

12.2 Pharmacodynamics

Cardiac Electrophysiology

The effects of trastuzumab on electrocardiographic (ECG) endpoints, including QTc interval duration, were evaluated in patients with HER2-positive solid tumors. Trastuzumab had no clinically relevant effect on the QTc interval duration and there was no apparent relationship between serum trastuzumab concentrations and change in QTcF interval duration in patients with HER2-positive solid tumors.

12.3 Pharmacokinetics

Trastuzumab exposure following subcutaneous administration of HERCEPTIN HYLECTA 600 mg every 3 weeks as compared to intravenous trastuzumab 8 mg/kg loading dose, 6 mg/kg maintenance every 3 weeks in the HannaH Study is shown in Table 6. The pharmacokinetic (PK) results for the co-primary endpoint, Ctrough pre-dose Cycle 8, showed non-inferiority of HERCEPTIN HYLECTA (78.7 mcg/mL) compared to intravenous trastuzumab (57.8 mcg/mL), with a geometric mean ratio of 1.3 (90% CI: 1.2–1.4).

A population PK model with parallel linear and nonlinear elimination from the central compartment was constructed using pooled HERCEPTIN HYLECTA and intravenous trastuzumab pharmacokinetic (PK) data from HannaH to describe the observed trastuzumab PK concentrations following HERCEPTIN HYLECTA subcutaneous administration and intravenous trastuzumab administration. Population PK predicted trastuzumab exposure are shown in Table 6.

Following subcutaneous administration of HERCEPTIN HYLECTA, trastuzumab concentrations were approximately at steady-state after the Cycle 7 dose with < 15% increase in concentration up to Cycle 13. The mean Ctrough at the pre-dose Cycle 18 in HERCEPTIN HYLECTA arm is similar to that of Cycle 13, suggesting no further increase after Cycle 13. The mean Cmax was 32% lower, and the mean AUC0-21 days following the Cycle 7 dose and Cycle 12 dose was approximately 10% and 20% higher, respectively, in the HERCEPTIN HYLECTA arm than in the intravenous trastuzumab arm.

Table 6 Trastuzumab Exposure (median with 5th-95th Percentiles) following Subcutaneous Administration of HERCEPTIN HYLECTA or Intravenous Trastuzumab
Trastuzumab Exposure |  | HERCEPTIN HYLECTA | Intravenous Trastuzumab
Ctrough (mcg/mL) | Cycle 1 | 28.2 (14.8–40.9) | 29.4 (5.8–59.5)
Ctrough (mcg/mL) | Cycle 7 | 75.0 (35.1–123) | 47.4 (5–114.7)
Cmax (mcg/mL) | Cycle 1 | 79.3 (56.1–109) | 178 (117–291)
Cmax (mcg/mL) | Cycle 7 | 149 (86.1–214) | 179 (107–309)
AUC0-21 days (mcg/mL∙day) | Cycle 1 | 1065 (718–1504) | 1373 (736–2245)
AUC0-21 days (mcg/mL∙day) | Cycle 7 | 2337 (1258–3478) | 1794 (673–3618)

General PK parameters of trastuzumab following subcutaneous administration of HERCEPTIN HYLECTA are shown in Table 7. Trastuzumab is estimated to reach concentrations that are < 1 mcg/mL by 7 months in at least 95% patients.

Table 7 PK parameters of Trastuzumab following Subcutaneous Administration of HERCEPTIN HYLECTA [Parameters represented as geometric mean (%CV) unless otherwise specified]
Absorption
Absolute Bioavailability | 0.77 (13)
First-order absorption rate, ka (day^-1) | 0.4 (2.92) [Residual standard error]
Tmax (day) | 3 (1-14) [Median (range)]
Distribution
Volume of Central Compartment (L) | 2.9 (19.1)
Elimination
Linear Elimination Clearance (L/day) | 0.11 (30)
Non-linear Elimination Vmax (mg/day) | 11.9 (19.9)
Non-linear Elimination Km (mg/L) | 33.9 (38.6)

Specific Populations

Body weight showed a statistically significant influence on PK. In patients with a body weight < 51 kg, mean steady state AUC of trastuzumab was about 80% higher after HERCEPTIN HYLECTA than after intravenous trastuzumab treatment, whereas in the highest BW group (> 90 kg) AUC was 20% lower after HERCEPTIN HYLECTA than after intravenous trastuzumab treatment. However, no body weight based dose adjustments are needed, as the exposure changes are not considered clinically relevant.

Drug Interaction Studies

There have been no formal drug interaction studies performed with trastuzumab in humans. Clinically significant interactions between trastuzumab and concomitant medications used in clinical trials have not been observed.

Paclitaxel and doxorubicin: Concentrations of paclitaxel and doxorubicin and their major metabolites (i.e., 6-α hydroxyl-paclitaxel [POH], and doxorubicinol [DOL], respectively) were not altered in the presence of trastuzumab when used as combination therapy in clinical trials. Trastuzumab concentrations were not altered as part of this combination therapy.

Docetaxel and carboplatin: When intravenous trastuzumab was administered in combination with docetaxel or carboplatin, neither the plasma concentrations of docetaxel or carboplatin nor the plasma concentrations of trastuzumab were altered.

Cisplatin and capecitabine: In a drug interaction substudy conducted in patients in Study BO18255, the pharmacokinetics of cisplatin, capecitabine and their metabolites were not altered when administered in combination with intravenous trastuzumab.

12.6 Immunogenicity

As with all therapeutic proteins, there is potential for immunogenicity. The detection of antibody formation is highly dependent on the sensitivity and specificity of the assay. Additionally, the observed incidence of antibody (including neutralizing antibody) positivity in an assay may be influenced by several factors including assay methodology, sample handling, timing of sample collection, concomitant medications, and underlying disease. For these reasons, comparison of the incidence of antibodies to HERCEPTIN HYLECTA and intravenous trastuzumab in the study described below with the incidence of antibodies in other studies or to other products may be misleading.

In the HannaH study, at a median follow-up exceeding 60 months, the incidence of treatment-induced/enhanced anti-trastuzumab antibodies was 10% (30/296) in patients treated with intravenous trastuzumab and 16% (47/295) in patients receiving HERCEPTIN HYLECTA. Neutralizing anti-trastuzumab antibodies were detected in post-baseline samples in 2/30 patients in the intravenous trastuzumab arm and 3/47 patients in the HERCEPTIN HYLECTA arm. The incidence of treatment-induced/enhanced anti-recombinant human hyaluronidase antibodies was 21% (62/295) in the HERCEPTIN HYLECTA arm. None of the patients who tested positive for anti-recombinant human hyaluronidase antibodies tested positive for neutralizing antibodies.

The clinical relevance of the development of anti-trastuzumab or anti-recombinant human hyaluronidase antibodies after treatment with HERCEPTIN HYLECTA is not known.

13 NONCLINICAL TOXICOLOGY

13.1 Carcinogenesis, Mutagenesis, Impairment of Fertility

HERCEPTIN HYLECTA contains trastuzumab and hyaluronidase.

Trastuzumab has not been tested for carcinogenicity potential.

No evidence of mutagenic activity was observed when trastuzumab was tested in the standard Ames bacterial and human peripheral blood lymphocyte mutagenicity assays at concentrations of up to 5000 mcg/mL. In an in vivo micronucleus assay, no evidence of chromosomal damage to mouse bone marrow cells was observed following bolus intravenous doses of up to 118 mg/kg of trastuzumab.

A fertility study was conducted in female cynomolgus monkeys at doses up to 25 times the weekly recommended human dose of 2 mg/kg of intravenous trastuzumab and has revealed no evidence of impaired fertility, as measured by menstrual cycle duration and female sex hormone levels.

Hyaluronidases are found in most tissues of the body. Long-term animal studies have not been performed to assess the carcinogenic or mutagenic potential of hyaluronidase. In addition, when hyaluronidase (recombinant human) was administered to cynomolgus monkeys for 39 weeks at dose levels up to 220,000 U/kg, which is > 670 times higher than the human dose, no evidence of toxicity to the male or female reproductive system was found through periodic monitoring of in-life parameters, e.g., semen analyses, hormone levels, menstrual cycles, and also from gross pathology, histopathology and organ weight data.

14 CLINICAL STUDIES

The comparability between HERCEPTIN HYLECTA administered subcutaneously and intravenous trastuzumab was established in the HannaH study. The HannaH study was conducted in patients with HER2 overexpressing breast cancer in the neoadjuvant and adjuvant settings with co-primary endpoints of pathological complete response (pCR) and the PK endpoint of Ctrough at cycle 7 [see Clinical Pharmacology (12.3)].

14.1 Adjuvant Breast Cancer

HERCEPTIN HYLECTA

HannaH

The HannaH study (NCT00950300) was a randomized, multicenter, open-label, clinical trial in 596 patients with HER2-positive operable or locally advanced breast cancer (LABC), including inflammatory breast cancer. HER2-positivity was defined as IHC 3+ or ISH+. Patients were randomized to receive 8 cycles of either HERCEPTIN HYLECTA or intravenous trastuzumab concurrently with chemotherapy (docetaxel followed by 5FU, epirubicin and cyclophosphamide), followed by surgery and continued therapy with HERCEPTIN HYLECTA or intravenous trastuzumab as treated prior to surgery, for an additional 10 cycles, to complete 18 cycles of therapy. HannaH was designed to demonstrate non-inferiority of treatment with HERCEPTIN HYLECTA versus intravenous trastuzumab based on co-primary PK and efficacy outcomes (trastuzumab Ctrough at pre-dose Cycle 8, and pCR rate at definitive surgery, respectively) [see Clinical Pharmacology 12.3]. EFS and OS were among other outcomes evaluated in this study. The majority of patients were white (69%) and the median age was 50 years (range: 24-81).

The analysis of the efficacy co-primary outcome, pCR, defined as absence of invasive neoplastic cells in the breast, resulted in rates of 45.4% (95% CI: 39.2, 51.7) in the HERCEPTIN HYLECTA arm and 40.7% (95% CI: 34.7, 46.9) in the intravenous trastuzumab arm.

Table 8: Summary of Pathological Complete Response (pCR) (HannaH)
 | HERCEPTIN HYLECTA (n=260) | Intravenous Trastuzumab (n=263)
pCR (absence of invasive neoplastic cells in breast [ypT0/is]) | 118 (45.4%) | 107 (40.7%)
Exact 95% CI for pCR Rate [CI for one sample binomial using Pearson-Clopper method] | (39.2; 51.7) | (34.7; 46.9)
Difference in pCR (SC minus IV arm) | 4.70
95% CI for Difference in pCR [Approximate 95% CI for difference of two rates using Hauck-Anderson method] | (-4.0; 13.4)

With a median follow-up exceeding 70 months, no difference in EFS and OS was observed in the final analysis between patients who received intravenous trastuzumab and those who received HERCEPTIN HYLECTA.

SafeHER

The SafeHER study (NCT01566721) was a prospective, two-cohort, non-randomized, multinational, open-label study designed to assess the overall safety and tolerability of HERCEPTIN HYLECTA with chemotherapy in 1864 patients with HER2-positive breast cancer. The secondary objectives include the evaluation of DFS and OS. HER2-positivity was defined as IHC 3+ or ISH+. Patients received a fixed dose of 600 mg HERCEPTIN HYLECTA every 3 weeks for a total of 18 cycles throughout the study. HERCEPTIN HYLECTA treatment was initiated either sequentially with chemotherapy, concurrently with chemotherapy, or without adjuvant chemotherapy, or in combination with neoadjuvant chemotherapy followed by trastuzumab therapy. The majority of treated patients were white (76%) and the median age was 54 years (range: 20-88).

In the primary safety analysis (median follow-up 23.7 months), no new safety signals were identified for HERCEPTIN HYLECTA. Safety and tolerability results, including in lower weight patients, were consistent with the known safety profile for HERCEPTIN HYLECTA and intravenous trastuzumab.

In the ITT population (n=1867), 126 patients (7%) had a DFS event (recurrence, contralateral invasive breast cancer or death) and 28 patients (1.5%) had an OS event at the time of clinical cut-off.

Intravenous Trastuzumab

The safety and efficacy of intravenous trastuzumab in women receiving adjuvant chemotherapy for HER2 overexpressing breast cancer were evaluated in an integrated analysis of two randomized, open-label, clinical trials (Studies NSABP B31 and NCCTG N9831) with a total of 4063 women at the protocol-specified final overall survival analysis, a third randomized, open-label, clinical trial (HERA Study) with a total of 3386 women at definitive DFS analysis for 1-year intravenous trastuzumab treatment versus observation, and a fourth randomized, open-label clinical trial with a total of 3222 patients (Study BCIRG006).

Studies NSABP B31 and NCCTG N9831

In Studies NSABP B31 and NCCTG N9831, breast tumor specimens were required to show HER2 overexpression (3+ by IHC) or gene amplification (by FISH). HER2 testing was verified by a central laboratory prior to randomization (Study NCCTG N9831) or was required to be performed at a reference laboratory (Study NSABP B31). Patients with a history of active cardiac disease based on symptoms, abnormal electrocardiographic, radiologic, or left ventricular ejection fraction findings or uncontrolled hypertension (diastolic > 100 mm Hg or systolic > 200 mm Hg) were not eligible.

Patients were randomized (1:1) to receive doxorubicin and cyclophosphamide followed by paclitaxel (AC→paclitaxel) alone or paclitaxel plus intravenous trastuzumab (AC→paclitaxel + intravenous trastuzumab). In both trials, patients received four 21-day cycles of doxorubicin 60 mg/m^2 and cyclophosphamide 600 mg/m^2. Paclitaxel was administered either weekly (80 mg/m^2) or every 3 weeks (175 mg/m^2) for a total of 12 weeks in Study NSABP B31; paclitaxel was administered only by the weekly schedule in Study NCCTG N9831. Intravenous trastuzumab was administered at 4 mg/kg on the day of initiation of paclitaxel and then at a dose of 2 mg/kg weekly for a total of 52 weeks. Intravenous trastuzumab treatment was permanently discontinued in patients who developed congestive heart failure, or persistent/recurrent LVEF decline [see Dosage and Administration (2.3)]. Radiation therapy, if administered, was initiated after the completion of chemotherapy. Patients with ER+ and/or PR+ tumors received hormonal therapy. The major efficacy outcome of the combined efficacy analysis was DFS, defined as the time from randomization to recurrence, occurrence of contralateral breast cancer, other second primary cancer, or death. An additional efficacy outcome measure was OS.

A total of 3752 patients were included in the joint efficacy analysis of DFS following a median follow-up of 2.0 years in the AC→paclitaxel + intravenous trastuzumab arm. The pre-planned final OS analysis from the joint analysis included 4063 patients and was performed when 707 deaths had occurred after a median follow-up of 8.3 years in the AC→paclitaxel + intravenous trastuzumab arm. The data from both arms in Study NSABP B31 and two of the three study arms in Study NCCTG N9831 were pooled for efficacy analyses. The patients included in the DFS analysis had a median age of 49 years (range, 22–80 years; 6% > 65 years), 84% were White, 7% Black, 4% Hispanic, and 4% Asian/Pacific Islander. Disease characteristics included 90% infiltrating ductal histology, 38% T1, 91% nodal involvement, 27% intermediate and 66% high grade pathology, and 53% ER+ and/or PR+ tumors.

HERA Study

In the HERA Study, breast tumor specimens were required to show HER2 overexpression (3+ by IHC) or gene amplification (by FISH) as determined at a central laboratory. Patients with node-negative disease were required to have ≥ T1c primary tumor. Patients with a history of congestive heart failure or LVEF < 55%, uncontrolled arrhythmias, angina requiring medication, clinically significant valvular heart disease, evidence of transmural infarction on ECG, poorly controlled hypertension (systolic > 180 mm Hg or diastolic > 100 mm Hg) were not eligible.

Patients were randomized (1:1:1) upon completion of definitive surgery, and at least 4 cycles of chemotherapy to receive no additional treatment, or 1 year of intravenous trastuzumab treatment or 2 years of intravenous trastuzumab treatment. Patients undergoing a lumpectomy had also completed standard radiotherapy. Patients with ER+ and/or PgR+ disease received systemic adjuvant hormonal therapy at investigator discretion. Intravenous trastuzumab was administered with an initial dose of 8 mg/kg followed by subsequent doses of 6 mg/kg once every 3 weeks. The major efficacy outcome measure was DFS, defined as in Studies NSABP B31 and NCCTG N9831.

HERA was designed to compare 1 and 2 years of three-weekly intravenous trastuzumab treatment versus observation in patients with HER2 positive EBC following surgery, established chemotherapy and radiotherapy (if applicable). A protocol specified interim efficacy analysis comparing one-year intravenous trastuzumab treatment to observation was performed at a median follow-up duration of 12.6 months in the intravenous trastuzumab. Among the 3386 patients randomized to the observation (n = 1693) and intravenous trastuzumab one-year (n = 1693) treatment arms, the median age was 49 years (range 21–80), 83% were White, and 13% were Asian. Disease characteristics: 94% infiltrating ductal carcinoma, 50% ER+ and/or PgR+, 57% node positive, 32% node negative, and in 11% of patients, nodal status was not assessable due to prior neo-adjuvant chemotherapy. Ninety-six percent (1055/1098) of patients with node-negative disease had high-risk features: among the 1098 patients with node-negative disease, 49% (543) were ER– and PgR–, and 47% (512) were ER+ and/or PgR+ and had at least one of the following high-risk features: pathological tumor size > 2 cm, Grade 2–3, or age < 35 years. Prior to randomization, 94% of patients had received anthracycline-based chemotherapy regimens.

After the DFS results comparing observation to one-year intravenous trastuzumab treatment were disclosed, a prospectively planned analysis that included comparison of one year versus two years of intravenous trastuzumab treatment at a median follow-up duration of 8 years was performed. Based on this analysis, extending intravenous trastuzumab treatment for a duration of two years did not show additional benefit over treatment for one year [Hazard Ratios of two-years intravenous trastuzumab versus one-year intravenous trastuzumab treatment in the ITT population for DFS = 0.99 (95% CI: 0.87, 1.13), p = 0.90 and OS = 0.98 (0.83, 1.15); p = 0.78].

BCIRG006 Study

In the BCIRG006 Study, breast tumor specimens were required to show HER2 gene amplification (FISH+ only) as determined at a central laboratory. Patients were required to have either node-positive disease, or node-negative disease with at least one of the following high-risk features: ER/PR-negative, tumor size > 2 cm, age < 35 years, or histologic and/or nuclear Grade 2 or 3. Patients with a history of CHF, myocardial infarction, Grade 3 or 4 cardiac arrhythmia, angina requiring medication, clinically significant valvular heart disease, poorly controlled hypertension (diastolic > 100 mm Hg), any T4 or N2, or known N3 or M1 breast cancer were not eligible.

Patients were randomized (1:1:1) to receive doxorubicin and cyclophosphamide followed by docetaxel (AC-T), doxorubicin and cyclophosphamide followed by docetaxel plus intravenous trastuzumab (AC-TH), or docetaxel and carboplatin plus intravenous trastuzumab (TCH). In both the AC-T and AC-TH arms, doxorubicin 60 mg/m^2 and cyclophosphamide 600 mg/m^2 were administered every 3 weeks for four cycles; docetaxel 100 mg/m^2 was administered every 3 weeks for four cycles. In the TCH arm, docetaxel 75 mg/m^2 and carboplatin (at a target AUC of 6 mg/mL/min as a 30- to 60-minute infusion) were administered every 3 weeks for six cycles. Intravenous trastuzumab was administered weekly (initial dose of 4 mg/kg followed by weekly dose of 2 mg/kg) concurrently with either T or TC, and then every 3 weeks (6 mg/kg) as monotherapy for a total of 52 weeks. Radiation therapy, if administered, was initiated after completion of chemotherapy. Patients with ER+ and/or PR+ tumors received hormonal therapy. DFS was the major efficacy outcome measure.

Among 3222 patients, the median age was 49 (range 22 to 74 years; 6% ≥ 65 years). Disease characteristics included 54% ER+ and/or PR+ and 71% node positive. Prior to randomization, all patients underwent primary surgery for breast cancer.

The results for DFS for the integrated analysis of Studies NSABP B31 and NCCTG N9831, HERA, and BCIRG006 and OS results for the integrated analysis of Studies NSABP B31 and NCCTG N9831, and HERA are presented in Table 9. For Studies NSABP B31 and NCCTG N9831, the duration of DFS following a median follow-up of 2.0 years in the AC→TH arm is presented in Figure 1, and the duration of OS after a median follow-up of 8.3 years in the AC→TH arm is presented in Figure 2. The duration of DFS for BCIRG006 is presented in Figure 3. For Studies NSABP B31 and NCCTG N9831, the OS hazard ratio was 0.64 (95% CI: 0.55, 0.74). At 8.3 years of median follow-up [AC→TH], the survival rate was estimated to be 86.9% in the AC→TH arm and 79.4% in the AC→T arm. The final OS analysis results from Studies NSABP B31 and NCCTG N9831 indicate that OS benefit by age, hormone receptor status, number of positive lymph nodes, tumor size and grade, and surgery/radiation therapy was consistent with the treatment effect in the overall population. In patients ≤ 50 years of age (n = 2197), the OS hazard ratio was 0.65 (95% CI: 0.52, 0.81) and in patients > 50 years of age (n = 1866), the OS hazard ratio was 0.63 (95% CI: 0.51, 0.78). In the subgroup of patients with hormone receptor-positive disease (ER-positive and/or PR-positive) (n = 2223), the hazard ratio for OS was 0.63 (95% CI: 0.51, 0.78). In the subgroup of patients with hormone receptor-negative disease (ER-negative and PR-negative) (n = 1830), the hazard ratio for OS was 0.64 (95% CI: 0.52, 0.80). In the subgroup of patients with tumor size ≤ 2 cm (n = 1604), the hazard ratio for OS was 0.52 (95% CI: 0.39, 0.71). In the subgroup of patients with tumor size > 2 cm (n = 2448), the hazard ratio for OS was 0.67 (95% CI: 0.56, 0.80).

Table 9 Efficacy Results from Adjuvant Treatment of Breast Cancer (Studies NSABP B31, NCCTG N9831, HERA, and BCIRG006)
 | DFS events | DFS Hazard ratio (95% CI) p-value | Deaths (OS events) | OS Hazard ratio p-value
Studies NSABP B31 and NCCTG N9831 [Studies NSABP B31 and NCCTG N9831 regimens: doxorubicin and cyclophosphamide followed by paclitaxel (AC→T) or paclitaxel plus intravenous trastuzumab (AC→TH).]
AC→TH (n = 1872) [Efficacy evaluable population, for the primary DFS analysis, following a median follow-up of 2.0 years in the AC→TH arm.] (n = 2031) [Efficacy evaluable population, for the final OS analysis, following 707 deaths (8.3 years of median follow-up in the AC→TH arm).] | 133 | 0.48, [Hazard ratio estimated by Cox regression stratified by clinical trial, intended paclitaxel schedule, number of positive nodes, and hormone receptor status.] (0.39, 0.59) p< 0.0001 [stratified log-rank test.] | 289 | 0.64, (0.55, 0.74) p< 0.0001
AC→T (n = 1880) (n = 2032) | 261 |  | 418
HERA [At definitive DFS analysis with median duration of follow-up of 12.6 months in the one-year intravenous trastuzumab treatment arm.]
Chemo→ Intravenous trastuzumab (n = 1693) | 127 | 0.54 (0.44, 0.67) p< 0.0001 [log-rank test.] | 31 | 0.75 p = NS [NS = non-significant.]
Chemo→ Observation (n = 1693) | 219 |  | 40
BCIRG006 [BCIRG006 regimens: doxorubicin and cyclophosphamide followed by docetaxel (AC→T) or docetaxel plus intravenous trastuzumab (AC→TH); docetaxel and carboplatin plus intravenous trastuzumab (TCH).]
TCH (n = 1075) | 134 | 0.67 (0.54 – 0.84) p=0.0006, [A two-sided alpha level of 0.025 for each comparison.] | 56
AC→TH (n = 1074) | 121 | 0.60 (0.48 – 0.76) p< 0.0001, | 49
AC→T (n = 1073) | 180 |  | 80
CI = confidence interval.

Figure 1 Duration of Disease-Free Survival in Patients with Adjuvant Treatment of Breast Cancer (Studies NSABP B31 and NCCTG N9831)

Figure 2 Duration of Overall Survival in Patients with Adjuvant Treatment of Breast Cancer (Studies NSABP B31 and NCCTG N9831)

Figure 3 Duration of Disease-Free Survival in Patients with Adjuvant Treatment of Breast Cancer (BCIRG006)

Exploratory analyses of DFS as a function of HER2 overexpression or gene amplification were conducted for patients in Study NCCTG N9831 and HERA, where central laboratory testing data were available. The results are shown in Table 10. The number of events in Study NCCTG N9831 was small with the exception of the IHC 3+/FISH+ subgroup, which constituted 81% of those with data. Definitive conclusions cannot be drawn regarding efficacy within other subgroups due to the small number of events. The number of events in HERA was adequate to demonstrate significant effects on DFS in the IHC 3+/FISH unknown and the FISH+/IHC unknown subgroups.

Table 10 Treatment Outcomes in Study NCCTG N9831 and HERA for Patients with HER2 Overexpression or Amplification
 | Study NCCTG N9831 |  | HERA [Median follow-up duration of 12.6 months in the one-year intravenous trastuzumab treatment arm.]
HER2 Assay Result [IHC by HercepTest, FISH by PathVysion (HER2/CEP17 ratio ≥ 2.0) as performed at a central laboratory.] | Number of Patients | Hazard Ratio DFS (95% CI) | Number of Patients | Hazard Ratio DFS (95% CI)
IHC 3+
FISH (+) | 1170 | 0.42 (0.27, 0.64) | 91 | 0.56 (0.13, 2.50)
FISH (−) | 51 | 0.71 (0.04, 11.79) | 8 | —
FISH Unknown | 51 | 0.69 (0.09, 5.14) | 2258 | 0.53 (0.41, 0.69)
IHC < 3+ / FISH (+) | 174 | 1.01 (0.18, 5.65) | 299 [All cases in this category in HERA were IHC 2+.] | 0.53 (0.20, 1.42)
IHC unknown / FISH (+) | — | — | 724 | 0.59 (0.38, 0.93)

14.2 Metastatic Breast Cancer

Intravenous Trastuzumab

The safety and efficacy of intravenous trastuzumab in the treatment of women with metastatic breast cancer were studied in a randomized, controlled clinical trial in combination with chemotherapy (H0648g, n=469 patients) and an open-label single agent clinical trial (H0649g, n=222 patients). Both trials studied patients with metastatic breast cancer whose tumors overexpress the HER2 protein. Patients were eligible if they had level 2 or 3 overexpression (based on a 0 to 3 scale) by immunohistochemical assessment of tumor tissue performed by a central testing lab.

Previously Untreated Metastatic Breast Cancer (H0648g)

H0648g was a multicenter, randomized, open-label clinical trial conducted in 469 women with metastatic breast cancer who had not been previously treated with chemotherapy for metastatic disease. Patients were randomized to receive chemotherapy alone or in combination with trastuzumab given intravenously as a 4 mg/kg loading dose followed by weekly doses of intravenous trastuzumab at 2 mg/kg. For those who had received prior anthracycline therapy in the adjuvant setting, chemotherapy consisted of paclitaxel (175 mg/m^2 over 3 hours every 21 days for at least six cycles); for all other patients, chemotherapy consisted of anthracycline plus cyclophosphamide (AC: doxorubicin 60 mg/m^2 or epirubicin 75 mg/m^2 plus 600 mg/m^2 cyclophosphamide every 21 days for six cycles). Sixty-five percent of patients randomized to receive chemotherapy alone in this study received intravenous trastuzumab at the time of disease progression as part of a separate extension study.

Based upon the determination by an Independent Response Evaluation Committee, the patients randomized to intravenous trastuzumab and chemotherapy experienced a significantly longer time to disease progression (TTP), a higher overall response rate (ORR), and a longer median duration of response as compared with patients randomized to chemotherapy alone. Patients randomized to intravenous trastuzumab and chemotherapy also had a longer median overall survival (OS) (see Table 11). These treatment effects were observed both in patients who received intravenous trastuzumab plus paclitaxel and in those who received intravenous trastuzumab plus AC; however the magnitude of the effects was greater in the paclitaxel subgroup.

Table 11: H0648g: Efficacy Results in First-Line Treatment for Metastatic Breast Cancer
 | Combined Results |  | Paclitaxel Subgroup |  | AC Subgroup
 | Intravenous Trastuzumab + All Chemotherapy (n=235) | All Chemotherapy (n=234) | Intravenous Trastuzumab + Paclitaxel (n=92) | Paclitaxel (n=96) | Intravenous Trastuzumab + AC [AC=Anthracycline (doxorubicin or epirubicin) and cyclophosphamide.] (n=143) | AC (n=138)
Time to Disease Progression (TTP)
Median (months) [Assessed by an independent Response Evaluation Committee.] , [Kaplan-Meier Estimate.] | 7.2 | 4.5 | 6.7 | 2.5 | 7.6 | 5.7
95% CI | 7, 8 | 4, 5 | 5, 10 | 2, 4 | 7, 9 | 5, 7
p-value [log-rank test.] | < 0.0001 |  | < 0.0001 |  | 0.002
Overall Response Rate (ORR)
Events (n) | 45 | 29 | 38 | 15 | 50 | 38
95% CI | 39, 51 | 23, 35 | 28, 48 | 8, 22 | 42, 58 | 30, 46
p-value [χ2-test.] | < 0.001 |  | < 0.001 |  | 0.10
Duration of Response (DoR)
Median (months), | 8.3 | 5.8 | 8.3 | 4.3 | 8.4 | 6.4
25%, 75% Quartile | 6, 15 | 4, 8 | 5, 11 | 4, 7 | 6, 15 | 4, 8
Overall Survival (OS)
Median (months) | 25.1 | 20.3 | 22.1 | 18.4 | 26.8 | 21.4
95% CI | 22, 30 | 17, 24 | 17, 29 | 13, 24 | 23, 33 | 18, 27
p-value | 0.05 |  | 0.17 |  | 0.16

Data from H0648g suggest that the beneficial treatment effects were largely limited to patients with the highest level of HER2 protein overexpression (3+) (see Table 12).

Table 12: Treatment Effects in H0648g as a Function of HER2 Overexpression or Amplification
HER2 Assay Result | Number of Patients (N) | Relative Risk [The relative risk represents the risk of progression or death in the trastuzumab plus chemotherapy arm versus the chemotherapy arm.] for Time to Disease Progression (95% CI) | Relative Risk for Mortality (95% CI)
CTA 2+ or 3+ | 469 | 0.49 (0.40, 0.61) | 0.80 (0.64, 1.00)
FISH (+) [FISH testing results were available for 451 of the 469 patients enrolled on study.] | 325 | 0.44 (0.34, 0.57) | 0.70 (0.53, 0.91)
FISH (−) | 126 | 0.62 (0.42, 0.94) | 1.06 (0.70, 1.63)
CTA 2+ | 120 | 0.76 (0.50, 1.15) | 1.26 (0.82, 1.94)
FISH (+) | 32 | 0.54 (0.21, 1.35) | 1.31 (0.53, 3.27)
FISH (−) | 83 | 0.77 (0.48, 1.25) | 1.11 (0.68, 1.82)
CTA 3+ | 349 | 0.42 (0.33, 0.54) | 0.70 (0.51, 0.90)
FISH (+) | 293 | 0.42 (0.32, 0.55) | 0.67 (0.51, 0.89)
FISH (−) | 43 | 0.43 (0.20, 0.94) | 0.88 (0.39, 1.98)

Previously Treated Metastatic Breast Cancer (Study H0649g)

Intravenous trastuzumab was studied as a single agent in a multicenter, open-label, single-arm clinical trial (Study H0649g) in patients with HER2 overexpressing MBC who had relapsed following one or two prior chemotherapy regimens for metastatic disease. Of 222 patients enrolled, 66% had received prior adjuvant chemotherapy, 68% had received two prior chemotherapy regimens for metastatic disease, and 25% had received prior myeloablative treatment with hematopoietic rescue. Patients were treated with a loading dose of 4 mg/kg IV followed by weekly doses of trastuzumab at 2 mg/kg IV.

The ORR (complete response + partial response), as determined by an independent Response Evaluation Committee, was 14%, with a 2% complete response rate and a 12% partial response rate. Complete responses were observed only in patients with disease limited to skin and lymph nodes. The overall response rate in patients whose tumors tested as CTA 3+ was 18% while in those that tested as CTA 2+, it was 6%.

14.3 Patient Experience

The PrefHER study (NCT01401166) was a randomized, multi-center, two-arm, cross-over trial conducted in 240 patients with HER2-positive breast cancer undergoing neoadjuvant or adjuvant treatment. One hundred twenty-one patients in arm A received 4 cycles of HERCEPTIN HYLECTA followed by 4 cycles of intravenous trastuzumab and 119 patients in arm B received 4 cycles of intravenous trastuzumab followed by 4 cycles of HERCEPTIN HYLECTA. Both arms received a total of 18 cycles. After Cycle 8, 199 of 231 patients (86%) reported preferring subcutaneous administration of HERCEPTIN HYLECTA over intravenous trastuzumab and the most common reason cited was administration required less time (179/231) in the clinic. After Cycle 8, 29 out of 231 patients (13%) reported preferring intravenous trastuzumab over HERCEPTIN HYLECTA and the most common reason was fewer local injection reactions. Three out of 231 patients (1%) had no preference for the route of administration. Nine out of 240 (3.8%) withdrew from treatment prior to completion of Cycle 8 and did not complete the post-study preference questionnaire.

16 HOW SUPPLIED/STORAGE AND HANDLING

HERCEPTIN HYLECTA (trastuzumab and hyaluronidase-oysk) injection for subcutaneous use supplied as a sterile, preservative-free, colorless to yellowish, clear to opalescent solution in a single-dose vial. The following configuration is available:

Individually packaged single-dose vials:

- HERCEPTIN HYLECTA 600 mg/10,000 units (NDC: 50242-077-01) providing 600 mg trastuzumab and 10,000 units hyaluronidase per 5 mL.

STORAGE AND HANDLING

Store HERCEPTIN HYLECTA vials in the refrigerator at 2°C to 8°C (36°F to 46°F) in the original carton to protect from light. Do not freeze. Do not shake. Once removed from the refrigerator, HERCEPTIN HYLECTA must be administered within 4 hours and should not be kept above 30°C (86°F).

17 PATIENT COUNSELING INFORMATION

Cardiomyopathy

- Advise patients to contact a health care professional immediately for any of the following: new onset or worsening shortness of breath, cough, swelling of the ankles/legs, swelling of the face, palpitations, weight gain of more than 5 pounds in 24 hours, dizziness or loss of consciousness [see Warnings and Precautions (5.1)].

Embryo-Fetal Toxicity [see Warnings and Precautions (5.2)]

- Advise pregnant women and females of reproductive potential that HERCEPTIN HYLECTA exposure during pregnancy or within 7 months prior to conception can result in fetal harm. Advise female patients to contact their healthcare provider with a known or suspected pregnancy [see Use in Specific Populations (8.1)].
- Advise females of reproductive potential to use effective contraception during treatment and for 7 months following the last dose of HERCEPTIN HYLECTA [see Use in Specific Populations (8.3)].
- Advise women who are exposed to HERCEPTIN HYLECTA during pregnancy or who become pregnant within 7 months following the last dose of HERCEPTIN HYLECTA that there is a pregnancy pharmacovigilance program that monitors pregnancy outcomes. Encourage these patients to report their pregnancy to Genentech [see Use in Specific Populations (8.1)].

Hypersensitivity and Administration-Related Reactions

- Advise patients to contact their healthcare provider immediately and to report any symptoms of hypersensitivity and administration-related reactions including dizziness, nausea, chills, fever, vomiting, diarrhea, urticaria, angioedema, breathing problems, or chest pain [see Warnings and Precautions (5.5)].

HERCEPTIN HYLECTA® [trastuzumab and hyaluronidase-oysk]

Manufactured by:
Genentech, Inc.
A Member of the Roche Group
1 DNA Way
South San Francisco, CA 94080-4990
US License No. 1048

HERCEPTIN HYLECTA is a registered trademark of Genentech, Inc.
©2024 Genentech, Inc.

PRINCIPAL DISPLAY PANEL - 600 mg and 10,000 units/5 mL Vial Carton

NDC 50242-077-01

Herceptin Hylecta®
(trastuzumab and
hyaluronidase-oysk) Injection

600 mg and
10,000 units/5 mL
(120 mg and 2,000 units/mL)

For Subcutaneous Use Only

Single-Dose Vial
Discard Unused Portion

1 vial

Rx only
Genentech

11025235